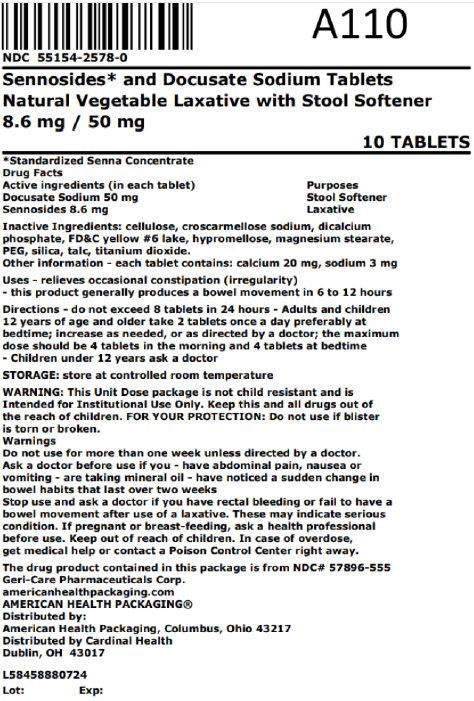 DRUG LABEL: Sennosides and Docusate Sodium
NDC: 55154-2578 | Form: TABLET
Manufacturer: Cardinal Health 107, LLC
Category: otc | Type: HUMAN OTC DRUG LABEL
Date: 20251030

ACTIVE INGREDIENTS: SENNOSIDES 8.6 mg/1 1; DOCUSATE SODIUM 50 mg/1 1
INACTIVE INGREDIENTS: MICROCRYSTALLINE CELLULOSE; CROSCARMELLOSE SODIUM; ANHYDROUS DIBASIC CALCIUM PHOSPHATE; FD&C YELLOW NO. 6 ALUMINUM LAKE; HYPROMELLOSE, UNSPECIFIED; MAGNESIUM STEARATE; POLYETHYLENE GLYCOL, UNSPECIFIED; SILICON DIOXIDE; TALC; TITANIUM DIOXIDE

Sennosides and Docusate Sodium Tablets
Natural Vegetable Laxative with Stool Softener
0462201/0825

Active ingredients(in each tablet)

Docusate Sodium 50 mg
Sennosides 8.6 mg

Purpose

Stool softener
Laxative

Uses

- relieves occasional constipation (irregularity)
- this product generally produces a bowel movement in 6 to 12 hours

Warnings

Do not use

- if you are now taking mineral oil, unless directed by a doctor
- laxative products for longer than 1 week unless directed by a doctor

Ask a doctor before use if you have

- stomach pain, nausea or vomiting
- noticed a sudden change in bowel habits that lasts over two weeks

Stop use and ask a doctor if

you have rectal bleeding or fail to have a bowel movement after use of a laxative.
These may indicate a serious condition.

If pregnant or breast-feeding,

ask a health professional before use.

Keep out of reach of children.

In case of overdose, get medical help or contact a Poison Control Center right away.

Directions

- do not exceed 8 tablets in 24 hours
- Adults and children 12 years of age and older take 2 tablets once a day preferably at bedtime; increase as needed, or as directed by a doctor; the maximum dose should be 4 tablets in the morning and 4 tablets at bedtime
- Children under 12 years ask a doctor

Other information

- each tablet contains: calcium 20 mg, sodium 3 mg. Very low sodium.
- store at 20°-25°C (68°-77°F); excursions permitted between 15°-30°C (59°-86°F).
- FOR YOUR PROTECTION: Do not use if blister is torn or broken.

Inactive ingredients

cellulose, croscarmellose sodium, dicalcium phosphate, FD&C yellow #6 lake, hypromellose, magnesium stearate, PEG, silica, talc, titanium dioxide.

The drug product contained in this package is from Geri-Care Pharmaceuticals Corp.

Distributed by:
American Health Packaging, Columbus, Ohio 43217 Product of India

Overbagged with 10 tablets per bag, NDC 55154-2578-0

WARNING: This Unit Dose package is not child resistant and is Intended for Institutional Use Only. Keep this and all drugs out of the reach of children.

Distributed By:

Cardinal Health

Dublin, OH 43017

L58458880724

762201
0462201/0825

Principal Display Panel

NDC 55154-2578-0

Sennosides* and Docusate Sodium Tablets

Natural Vegetable Laxative with Stool Softener

8.6 mg / 50 mg

10 TABLETS